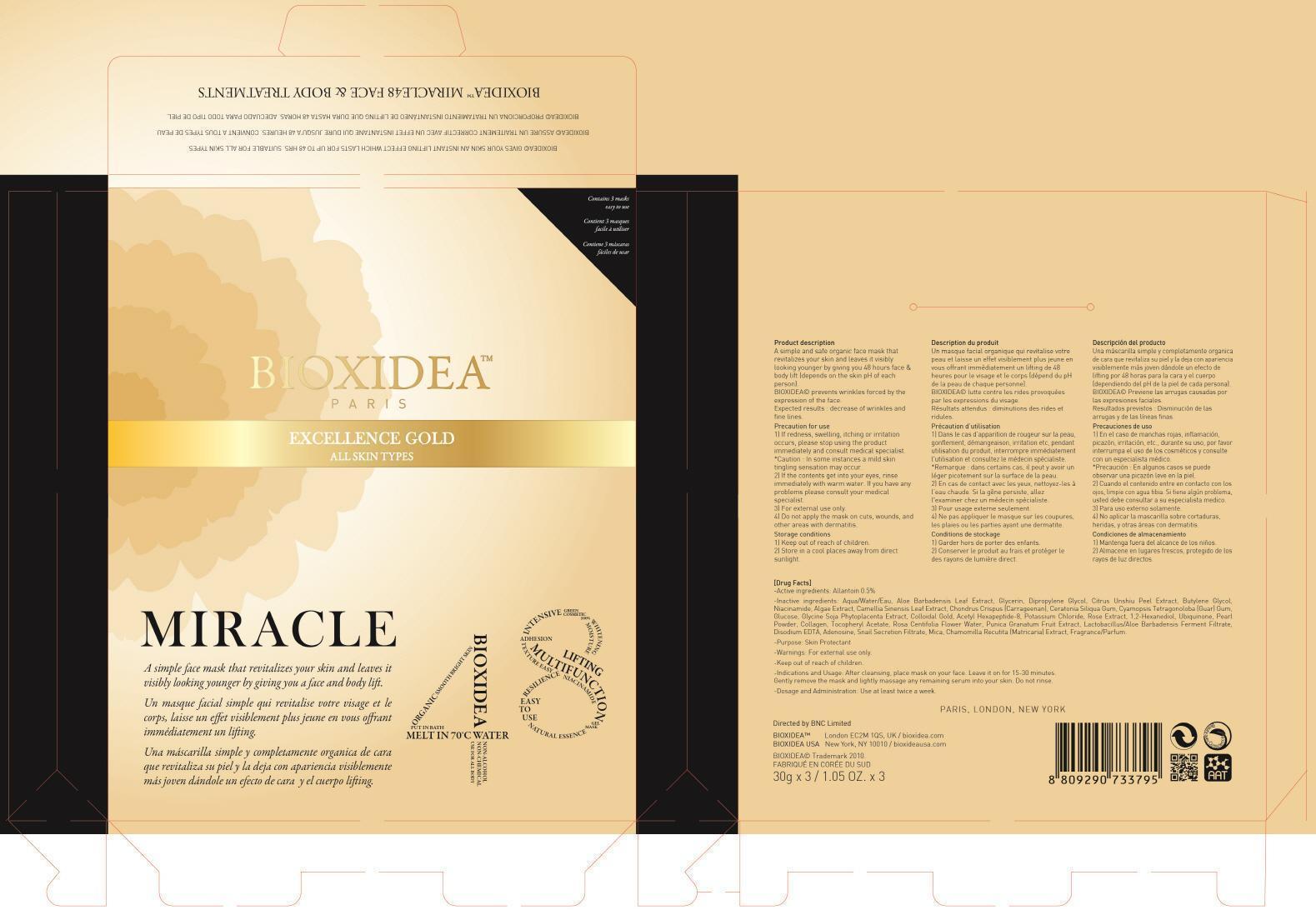 DRUG LABEL: BIOXIDEA MIRACLE 48 EXCELLENCE GOLD MASK
NDC: 69133-020 | Form: GEL
Manufacturer: Cosmetics Institute Technology Co., Ltd.
Category: otc | Type: HUMAN OTC DRUG LABEL
Date: 20141203

ACTIVE INGREDIENTS: Allantoin 0.15 g/3 1
INACTIVE INGREDIENTS: Water; Glycerin

ACTIVE INGREDIENT

Active ingredient: Allantoin 0.5%

INACTIVE INGREDIENT

Inactive ingredients:
Aqua/Water/Eau, Aloe Barbadensis Leaf Extract, Glycerin, Dipropylene Glycol, Citrus Unshiu Peel Extract, Butylene Glycol, Niacinamide, Algae Extract, Camellia Sinensis Leaf Extract, Chondrus Crispus (Carrageenan), Ceratonia Siliqua Gum, Cyamopsis Tetragonoloba (Guar) Gum, Glucose, Glycine Soja Phytoplacenta Extract, Colloidal Gold, Acetyl Hexapeptide-8, Potassium Chloride, Rose Extract, 1,2-Hexanediol, Ubiquinone, Pearl Powder, Collagen, Tocopheryl Acetate, Rosa Centifolia Flower Water, Punica Granatum Fruit Extract, Lactobacillus/Aloe Barbadensis Ferment Filtrate, Disodium EDTA, Adenosine, Snail Secretion Filtrate, Mica, Chamomilla Recutita (Matricaria) Extract, Fragrance/Parfum

PURPOSE

Purpose: Skin Protectant

WARNINGS

Warnings: For external use only.

KEEP OUT OF REACH OF CHILDREN

INDICATIONS & USAGE

Indications and Usage: After cleansing, place mask on your face. Leave it on for 20-30 minutes. Gently remove the mask and lightly massage any remaining serum into your skin. Do not rinse.

DOSAGE & ADMINISTRATION

Dosage and Administration: Use at least twice a week.